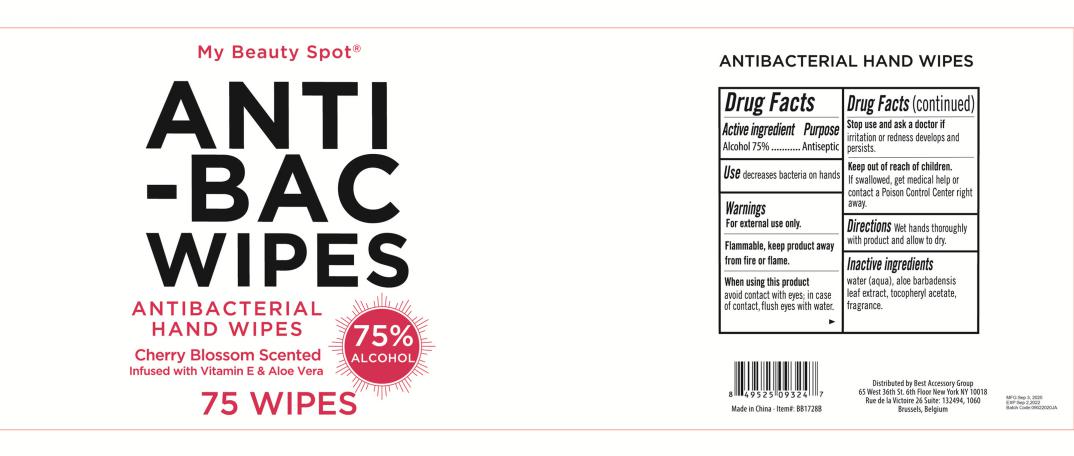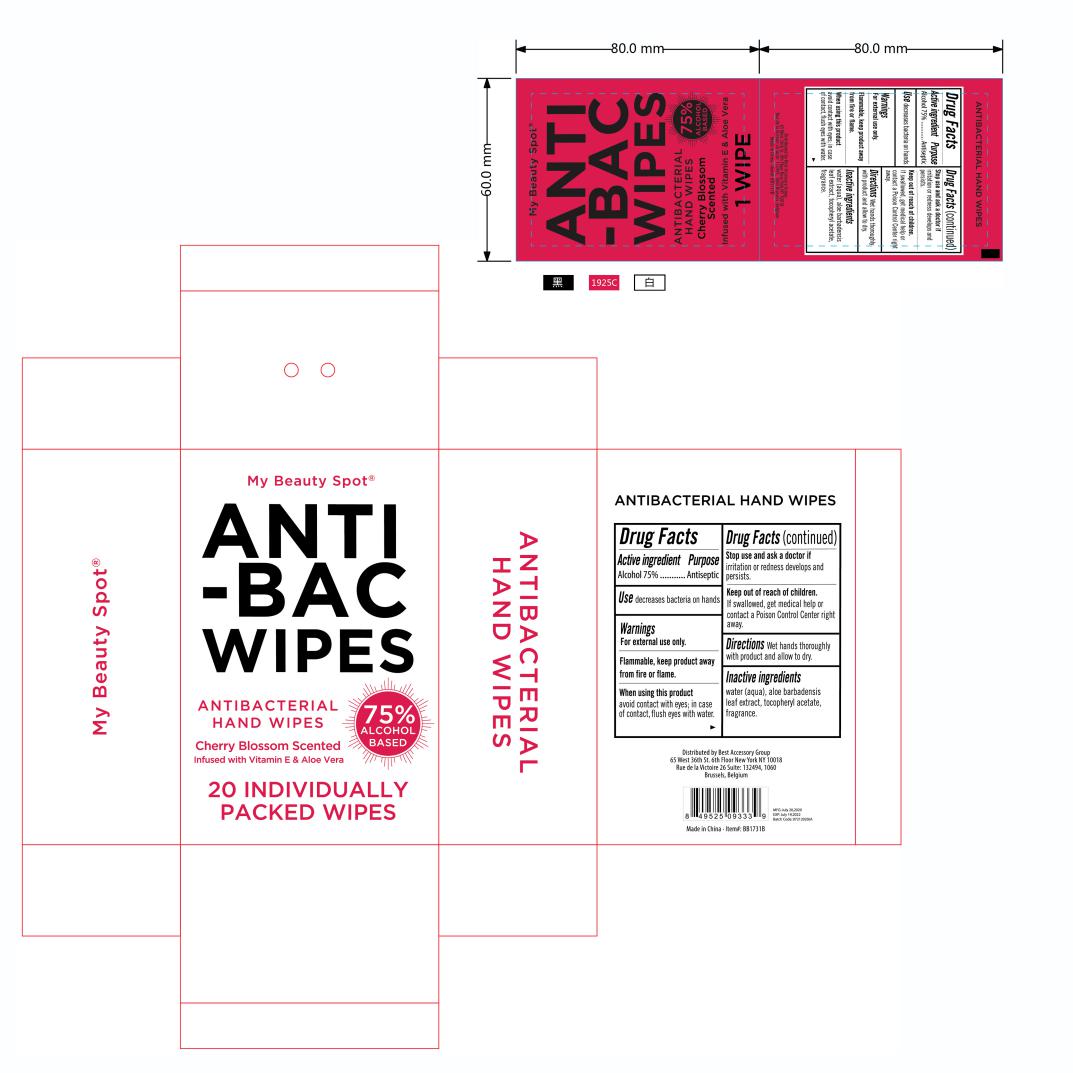 DRUG LABEL: BB1720B ANTIBACTERIAL HAND WIPES CHERRY BLOSSOM SCENTED
NDC: 78936-008 | Form: SWAB
Manufacturer: Hangzhou Caring Cleaning Commodity Co.,Ltd
Category: otc | Type: HUMAN OTC DRUG LABEL
Date: 20200904

ACTIVE INGREDIENTS: ALCOHOL 75 g/100 g
INACTIVE INGREDIENTS: ALOE VERA LEAF; ALPHA-TOCOPHEROL ACETATE; WATER; FRAGRANCE LAVENDER & CHIA F-153480

BB1720B ANTIBACTERIAL HAND WIPES CHERRY BLOSSOM SCENTED

Active Ingredient(s)

Alcohol 75%

Purpose

Antiseptic

Use

Decreases bacteria on hands.

Warnings

For external use only.

Flammable, keep away from fire or flame.

When using this product

Avoid contact with eyes; in case of contact, flush eyes with water

Stop use and ask a doctor if irritation or redness develops and persists.

Keep out of reach of children. If swallowed, get medical help or contact a Poison Control Center right away.

Directions

Wet hands thoroughly with product and allow to dry

Inactive ingredients

Water,Aloe Barbadensis Leaf Extract,Tocopheryl Acetate,Fragrance

Package Label - Principal Display Panel

75 POUCH IN 1 PAIL NDC: 78936-008-02

20 POUCH IN 1 BOX NDC: 78936-008-03